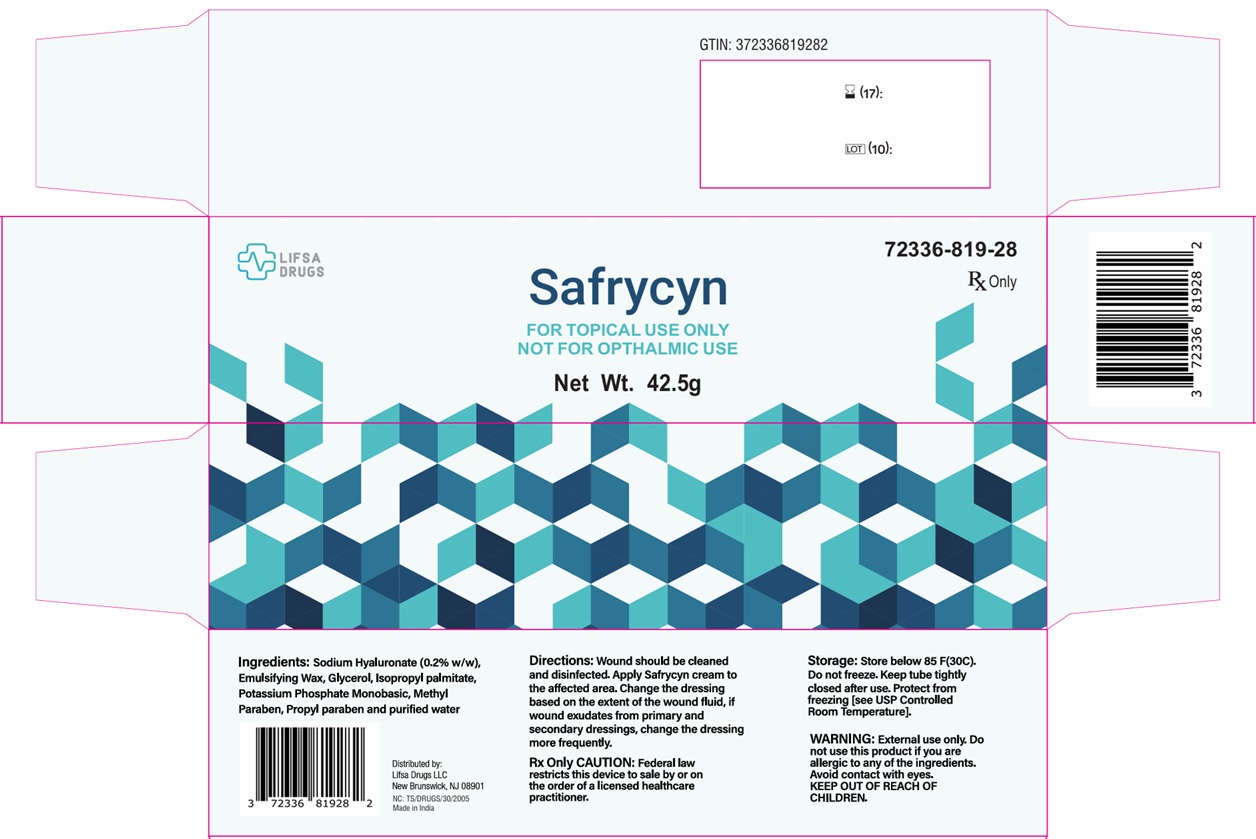 DRUG LABEL: Safrycyn WOUND CREAM DRESSING WITH HYALURONIC ACID
NDC: 72336-819
Manufacturer: Lifsa Drugs LLC
Category: other | Type: PRESCRIPTION MEDICAL DEVICE LABEL
Date: 20250801
INACTIVE INGREDIENTS: HYALURONATE SODIUM; MICROCRYSTALLINE WAX; GLYCERIN; ISOPROPYL PALMITATE; MONOBASIC POTASSIUM PHOSPHATE; METHYLPARABEN; PROPYLPARABEN; WATER

Safrycyn

DESCRIPTION: Safrycyn is a soothing wound Cream that is formulated for the dressing and management of superficial wounds, minor abrasions, pressure ulcers stage II - IV, 1st and 2nd degree burns, including sunburns, and radiation dermatitis. When applied properly to a wound hyaluronic acid adheres to tissue to prevent damage while supplying moisture to the cells. Proven therapeutic moisturizers, lipids and glycerin and relieves dryness

INDICATIONS FOR USE

Under the supervision of a healthcare professional, Safrycyn Cream is indicated to manage and relieve the burning, itching and pain experienced with various types of dermatoses, including atopic dermatitis, allergic contact dermatitis and radiation dermatitis. Safrycyn Cream also helps to relieve dry, waxy skin by maintaining a moist wound and skin environment, which is beneficial to the healing process.

DESCRIPTION

Safrycyn Cream is a non-sterile, off-white, low odor, fragrance free, topical product. The Safrycyn Cream forms a physical barrier that helps to maintain a moist wound and skin environment. Safrycyn Cream is a prescription medical device.

CONTRAINDICATIONS

Safrycyn Cream is contraindicated in persons with a known hypersensitivity to any of the components of the formulation.

WARNINGS

External use only. Do not use this product if you are allergic to any of the ingredients. Avoid contact with eyes. KEEP OUT OF REACH OF CHILDREN.

FOR TOPICAL USE ONLY

NOT FOR OPTHALMIC USE

PRECAUTIONS AND OBSERVATIONS

• Safrycyn Cream does not contain a sunscreen and should not be used prior to extended exposure to the sun.
• If clinical signs of infection are present, appropriate treatment should be initiated; use of Safrycyn Cream may be continued during the anti-infective therapy.

INSTRUCTIONS FOR USE

Wound should be cleaned and disinfected. Apply Safrycyn cream to the affected area. Change the dressing based on the extent of the wound fluid, if wound exudates from primary and secondary dressings, change the dressing more frequently.

INGREDIENTS

Sodium Hyaluronate (0.2% w/w), Emulsifying Wax, Glycerol, Isopropyl palmitate, Potassium Phosphate Monobasic, Methyl Paraben, Propyl paraben and purified water

HOW SUPPLIED

Safrycyn Cream is available in 42.5 grams Tube.

Rx Only CAUTION: Federal law restricts this device to sale by or on the order of a licensed healthcare practitioner.

Storage: Store below 85° F(30°C). Do not freeze. Keep tube tightly closed after use. Protect from freezing [see USP Controlled Room Temperature].

Distributed by:
Lifsa Drugs LLC
New Brunswick, NJ 08901

NC: TS/DRUGS/30/2005

Made in India